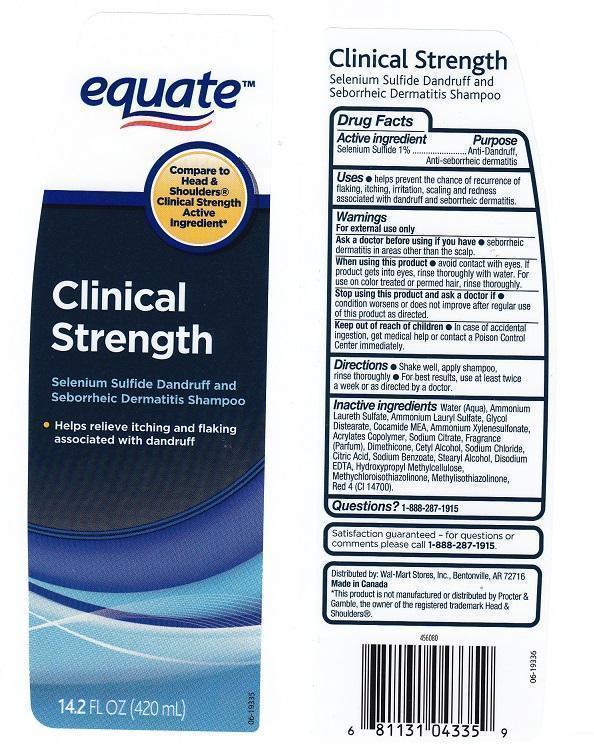 DRUG LABEL: EQUATE
NDC: 49035-918 | Form: LIQUID
Manufacturer: WAL-MART STORES INC
Category: otc | Type: HUMAN OTC DRUG LABEL
Date: 20140818

ACTIVE INGREDIENTS: SELENIUM SULFIDE 10 mg/1 mL
INACTIVE INGREDIENTS: WATER; AMMONIUM LAURETH-3 SULFATE; AMMONIUM LAURYL SULFATE; GLYCOL DISTEARATE; COCO MONOETHANOLAMIDE; AMMONIUM XYLENESULFONATE; METHACRYLIC ACID - METHYL METHACRYLATE COPOLYMER (1:1); SODIUM CITRATE; DIMETHICONE; CETYL ALCOHOL; SODIUM CHLORIDE; CITRIC ACID MONOHYDRATE; SODIUM BENZOATE; STEARYL ALCOHOL; EDETATE DISODIUM; HYPROMELLOSES; METHYLCHLOROISOTHIAZOLINONE; METHYLISOTHIAZOLINONE; FD&C RED NO. 4

DRUG FACTS

ACTIVE INGREDIENT

SELENIUM SULFIDE 1%

PURPOSE

ANTI-DANDRUFF, ANTI-SEBORRHEIC DERMATITIS

USES

HELPS PREVENT THE CHANCE OF RECURRENCE OF FLAKING, ITCHING, IRRITATION, SCALING AND REDNESS ASSOCIATED WITH DANDRUFF AND SEBORRHEIC DERMATITIS

WARNINGS

FOR EXTERNAL USE ONLY

ASK A DOCTOR BEFORE USING IF YOU HAVE

SEBHORREIC DERMATITIS IN AREAS OTHER THAN THE SCALP

WHEN USING THIS PRODUCT

AVOID CONTACT WITH EYES. IF PRODUCT GETS INTO EYES, RINSE THOROUGHLY WITH WATER. FOR USE ON COLOR TREATED OR PERMED HAIR, RINSE THOROUGHLY

STOP USING THIS PRODUCT AND ASK A DOCTOR IF

CONDITION WORSENS OR DOES NOT IMPROVE AFTER REGULAR USE OF THIS PRODUCT AS DIRECTED

KEEP OUT OF REACH OF CHILDREN

IN CASE OF ACCIDENTAL INGESTION, GET MEDICAL HELP OR CONTACT A POISON CONTROL CENTER IMMEDIATELY

DIRECTIONS

- SHAKE WELL, APPLY SHAMPOO, RINSE THOROUGHLY
- FOR BEST RESULTS, USE AT LEAST TWICE A WEEK OR AS DIRECTED BY A DOCTOR

INACTIVE INGREDIENTS

WATER (AQUA), AMMONIUM LAURETH SULFATE, AMMONIUM LAURYL SULFATE, GLYCOL DISTEARATE, COCAMIDE MEA, AMMONIUM XYLENESULFONATE, ACRYLATES COPOLYMER, SODIUM CITRATE, FRAGRANCE (PARFUM), DIMETHICONE, CETYL ALCOHOL, SODIUM CHLORIDE, CITRIC ACID, SODIUM BENZOATE, STEARYL ALCOHOL, DISODIUM EDTA, HYDROXYPROPYL METHYLCELLULOSE, METHYLCHLOROISOTHIAZOLINONE, METHYLISOTHIAZOLINONE, RED 4 (CI 14700)

QUESTIONS?

1-888-287-1915